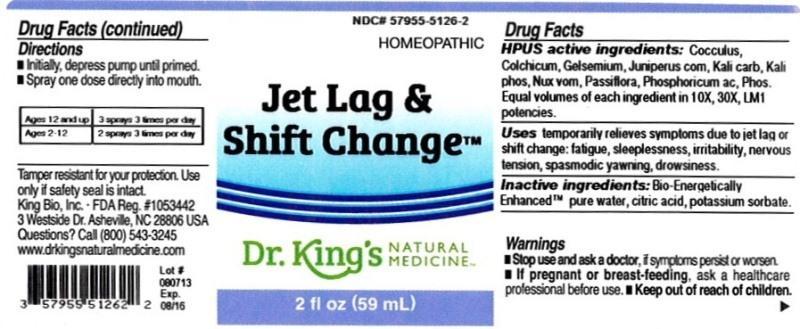 DRUG LABEL: Jet Lag and Shift Change
NDC: 57955-5126 | Form: LIQUID
Manufacturer: King Bio Inc.
Category: homeopathic | Type: HUMAN OTC DRUG LABEL
Date: 20131009

ACTIVE INGREDIENTS: ANAMIRTA COCCULUS SEED 10 [hp_X]/59 mL; COLCHICUM AUTUMNALE BULB 10 [hp_X]/59 mL; GELSEMIUM SEMPERVIRENS ROOT 10 [hp_X]/59 mL; JUNIPER BERRY 10 [hp_X]/59 mL; POTASSIUM CARBONATE 10 [hp_X]/59 mL; POTASSIUM PHOSPHATE, DIBASIC 10 [hp_X]/59 mL; STRYCHNOS NUX-VOMICA SEED 10 [hp_X]/59 mL; PASSIFLORA INCARNATA FLOWERING TOP 10 [hp_X]/59 mL; PHOSPHORIC ACID 10 [hp_X]/59 mL; PHOSPHORUS 10 [hp_X]/59 mL
INACTIVE INGREDIENTS: WATER; CITRIC ACID MONOHYDRATE; POTASSIUM SORBATE

Jet Lag and Shift Change™

Drug Facts

___________________________________________________________________________________________________________________

HPUS active ingredients: Cocculus indicus, Colchicum autumnale, Gelsemium sempervirens, Juniperus communis, Kali carbonicum, Kali phosphoricum, Nux vomica, Passiflora incarnata, Phosphoricum acidum, Phosphorus. Equal volumes of each ingredient in 10X, 30X, LM1 potencies.

INDICATIONS AND USAGE

Uses temporarily relieves symptoms due to jet lag or shift change: fatigue, sleeplessness, irritability, nervous tension, spasmodic yawning, drowsiness.

INACTIVE INGREDIENT

Inactive ingredients: Bio-Energetically Enhanced™ pure water base, citric acid, potassium sorbate.

Warnings

- Stop use and ask your doctor if symptoms persist or worsen.
- If pregnant or breast-feeding, ask a healthcare professional before use.

- Keep out of reach of children.

Directions

- Initially, depress pump until primed.
- Spray one dose directly into mouth.

Ages 12 and up: 3 sprays 3 times per day.

Ages 2-12: 2 sprays 3 times per day.

OTHER SAFETY INFORMATION

Tamper resistant for your protection. Use only if safety seal is intact.

PURPOSE

Uses temporarily relieves symptoms due to jet lag or shift change:

- fatigue
- sleeplessness
- irritability
- nervous tension
- spasmodic yawning
- drowsiness.